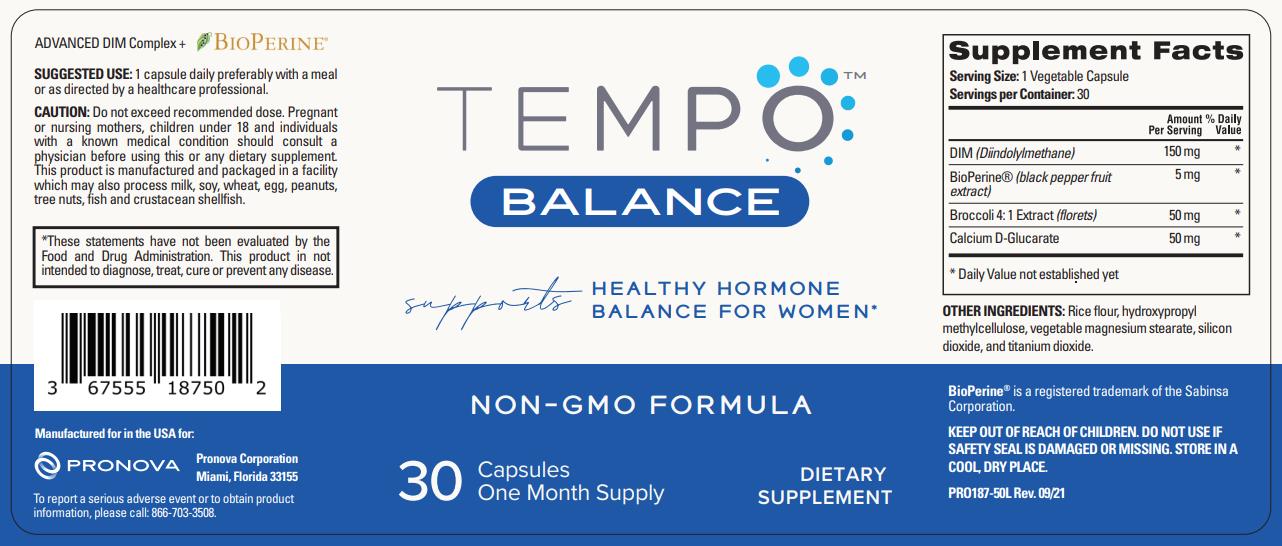 DRUG LABEL: TEMPO BALANCE
NDC: 67555-189 | Form: CAPSULE
Manufacturer: Pronova Corporation
Category: other | Type: DIETARY SUPPLEMENT
Date: 20230421

ACTIVE INGREDIENTS: 3,3'-DIINDOLYLMETHANE 150 mg/1 1; PIPERINE 5 mg/1 1; BROCCOLI 50 mg/1 1; CALCIUM SACCHARATE ANHYDROUS 50 mg/1 1
INACTIVE INGREDIENTS: BROWN RICE; HYPROMELLOSE, UNSPECIFIED; MAGNESIUM STEARATE; SILICON DIOXIDE; TITANIUM DIOXIDE

TEMPOTM BALANCE

STATEMENT OF IDENTITY

Supplement Facts
Serving Size: 1 Vegetable Capsule
Servings per Container: 30
 | Amount; Per Serving | % Daily; Value
DIM (Diindolylmethane) | 150 mg | *
BioPerine® (black pepper fruit extract) | 5 mg | *
Broccoli 4: 1 Extract (florets) | 50 mg | *
Calcium D-Glucarate | 50 mg | *
* Daily Value not established yet

OTHER INGREDIENTS: Rice flour, hydroxypropyl methylcellulose, vegetable magnesium stearate, silicon dioxide, and titanium dioxide.

BioPerine® is a registered trademark of the Sabinsa Corporation.

KEEP OUT OF REACH OF CHILDREN. DO NOT USE IF SAFETY SEAL IS DAMAGED OR MISSING. STORE IN A COOL, DRY PLACE.

DOSAGE AND ADMINISTRATION

SUGGESTED USE: 1 capsule daily preferably with a meal or as directed by a healthcare professional.

PRECAUTIONS

CAUTION: Do not exceed recommended dose. Pregnant or nursing mothers, children under 18 and individuals with a known medical condition should consult a physician before using this or any dietary supplement. This product is manufactured and packaged in a facility which may also process milk, soy, wheat, egg, peanuts, tree nuts, fish and crustacean shellfish.

*These statements have not been evaluated by the Food and Drug Administration. This product in not intended to diagnose, treat, cure or prevent any disease.

Manufactured for in the USA for:

Pronova Corporation
Miami, Florida 33155

To report a serious adverse event or to obtain product information, please call: 866-703-3508.

HEALTH CLAIM

supports HEALTHY HORMONE BALANCE FOR WOMEN*

NON-GMO FORMULA

DIETARY SUPPLEMENT

One Month Supply

ADVANCED DIM Complex + BIOPERINE®